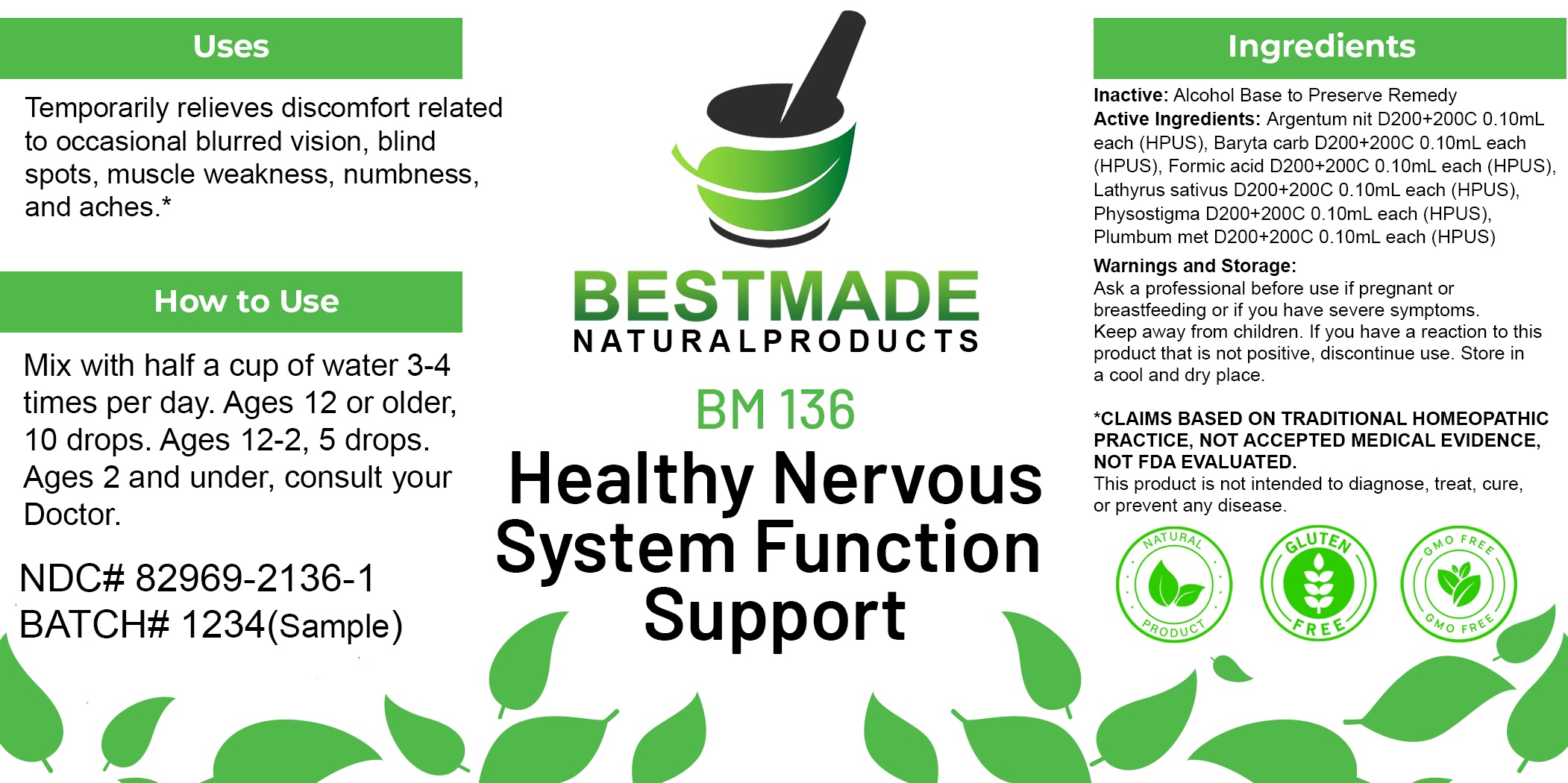 DRUG LABEL: Bestmade Natural Products BM136
NDC: 82969-2136 | Form: LIQUID
Manufacturer: Bestmade Natural Products
Category: homeopathic | Type: HUMAN OTC DRUG LABEL
Date: 20250212

ACTIVE INGREDIENTS: LATHYRUS SATIVAS SEED 30 [hp_C]/30 [hp_C]; FORMICA RUFA 30 [hp_C]/30 [hp_C]; LEAD 30 [hp_C]/30 [hp_C]; BARIUM CARBONATE 30 [hp_C]/30 [hp_C]; PHYSOSTIGMA VENENOSUM SEED 30 [hp_C]/30 [hp_C]; SILVER NITRATE 30 [hp_C]/30 [hp_C]
INACTIVE INGREDIENTS: ALCOHOL 30 [hp_C]/30 [hp_C]

BM136

DOSAGE AND ADMINISTRATION

How to Use

Mix with half a cup of water 3-4 times per day. Ages 12 or older, 10 drops. Ages 12-2, 5 drops. Ages 2 and under, consult your Doctor.

Inactive:

Alcohol Base to Preserve Product

ACTIVE INGREDIENTS

Argentum nit D200+200C 0.10mL each (HPUS), Baryta carb D200+200C 0.10mL each (HPUS), Formic acid D200+200C 0.10mL each (HPUS), Lathyrus sativus D200+200C 0.10mL each (HPUS), Physostigma D200+200C 0.10mL each (HPUS), Plumbum met D200+200C 0.10mL each (HPUS)

Uses
Temporarily relieves discomfort related to occasional blurred vision. blind spots, muscle weakness, numbness. and aches.*

Uses
Temporarily relieves discomfort related to occasional blurred vision. blind spots, muscle weakness, numbness. and aches.*

KEEP OUT OF REACH OF CHILDREN

Warnings and Storage:

Ask a professional before use if pregnant or breastfeeding or if you have severe symptoms.

Keep away from children. If you have a reaction to this product that is not positive, discontinue use. Store in a cool and dry place

*CLAIMS BASED ON TRADITIONAL HOMEOPATHIC PRACTICE, NOT ACCEPTED MEDICAL EVIDENCE NOT FDA EVALUATED.
This product is not intended to diagnose, treat, cure, or prevent any disease.

Warnings and Storage:

Ask a professional before use if pregnant or breastfeeding or if you have severe symptoms.

Keep away from children. If you have a reaction to this product that is not positive, discontinue use. Store in a cool and dry place

*CLAIMS BASED ON TRADITIONAL HOMEOPATHIC PRACTICE, NOT ACCEPTED MEDICAL EVIDENCE NOT FDA EVALUATED.
This product is not intended to diagnose, treat, cure, or prevent any disease.

Entire package label